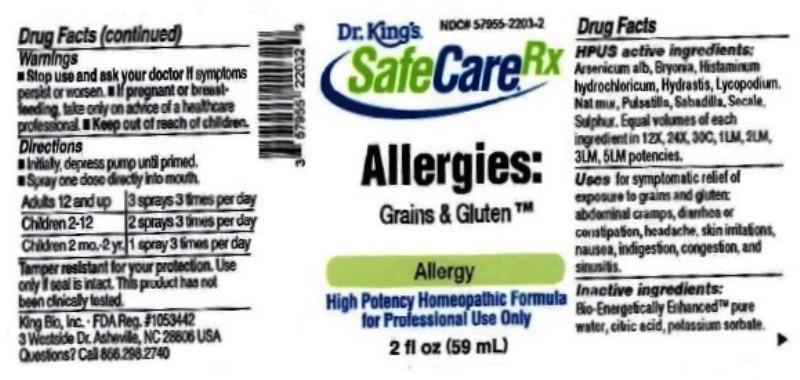 DRUG LABEL: Allergies Grains and Gluten
NDC: 57955-2203 | Form: LIQUID
Manufacturer: King Bio Inc.
Category: homeopathic | Type: HUMAN OTC DRUG LABEL
Date: 20161206

ACTIVE INGREDIENTS: ARSENIC TRIOXIDE 12 [hp_X]/59 mL; BRYONIA ALBA ROOT 12 [hp_X]/59 mL; HISTAMINE DIHYDROCHLORIDE 12 [hp_X]/59 mL; GOLDENSEAL 12 [hp_X]/59 mL; LYCOPODIUM CLAVATUM SPORE 12 [hp_X]/59 mL; SODIUM CHLORIDE 12 [hp_X]/59 mL; PULSATILLA VULGARIS 12 [hp_X]/59 mL; SCHOENOCAULON OFFICINALE SEED 12 [hp_X]/59 mL; CLAVICEPS PURPUREA SCLEROTIUM 12 [hp_X]/59 mL; SULFUR 12 [hp_X]/59 mL
INACTIVE INGREDIENTS: WATER; ANHYDROUS CITRIC ACID; POTASSIUM SORBATE

Allergies: Grains & Gluten™

ACTIVE INGREDIENT

Drug Facts__________________________________________________________________________________________________________

HPUS activeingredients: Arsenicum album, Bryonia, Histaminum hydrochloricum, Hydrastis canadensis, Lycopodium clavatum, Natrum muriaticum, Pulsatilla, Sabadilla, Secale cornutum, Sulphur. Equal volumes of each ingredient in 12X, 24X, 30C, 1LM, 2LM, 3LM, 5LM potencies.

INDICATIONS AND USAGE

Uses for symptomatic relief of exposure to grains and gluten: abdominal cramps, diarrhea or constipation, headache, skin irritations, nausea, indigestion, congestion, and sinusitis.

Inactive Ingredients:

Bio-Energetically Enhanced™ pure water, citric acid and potassium sorbate.

Warnings

- Stop use and ask your doctor if symptoms persist or worsen.
- If pregnant or breast-feeding, take only on advice of a healthcare professional.

- Keep out of reach of children.

Directions

- Initially, depress pump until primed.
- Spray one dose directly into mouth.
- Adults 12 and up: 3 sprays 3 times per day.
- Children 2-12: 2 sprays 3 times per day.
- Children 2 mo-2yr: 1 spray 3 times per day.

OTHER SAFETY INFORMATION

Tamper resistant for your protection. Use only if safety seal is intact. This product has not been clinically tested.

PURPOSE

Uses for symptomatic relief of exposure to grains and gluten:

- abdominal cramps
- diarrhea or constipation
- headache
- skin irritations
- nausea
- indigestion
- congestion
- sinusitis